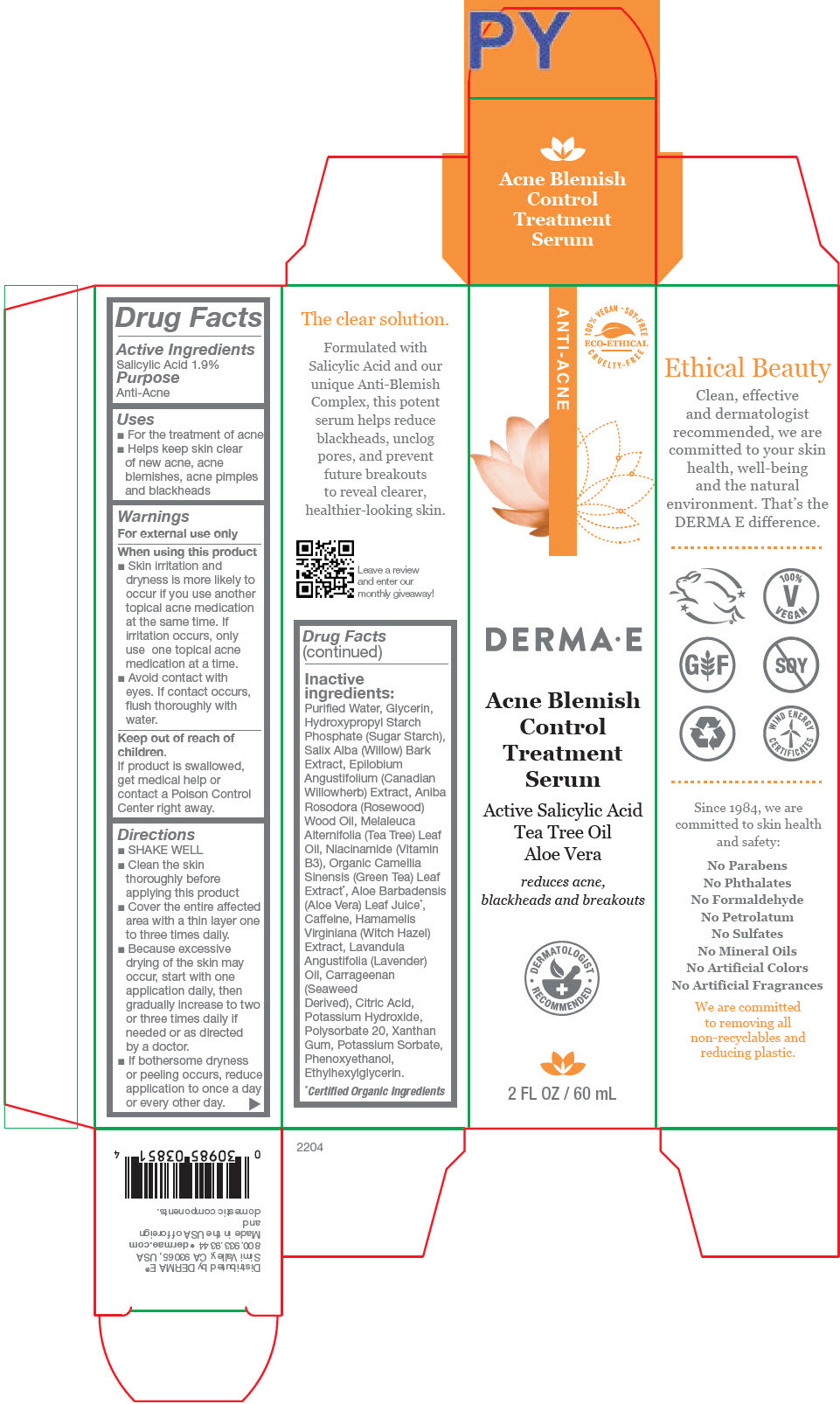 DRUG LABEL: Derma E Acne Blemish Control Treatment Serum
NDC: 54108-3851 | Form: LIQUID
Manufacturer: derma e
Category: otc | Type: HUMAN OTC DRUG LABEL
Date: 20240430

ACTIVE INGREDIENTS: SALICYLIC ACID 190 mg/1 mL
INACTIVE INGREDIENTS: WATER; ALOE VERA LEAF; GLYCERIN; EPILOBIUM ANGUSTIFOLIUM WHOLE; POTASSIUM HYDROXIDE; HYDROXYPROPYL CORN AMYLOPECTIN, PHOSPHATE CROSSLINKED (4000 MPA.S AT 5%); PHENOXYETHANOL; NIACINAMIDE; CARRAGEENAN; POLYSORBATE 20; TEA TREE OIL; XANTHAN GUM; CITRIC ACID MONOHYDRATE; ETHYLHEXYLGLYCERIN; POTASSIUM SORBATE; HAMAMELIS VIRGINIANA TOP; GREEN TEA LEAF; CAFFEINE; LAVENDER OIL; SALIX ALBA BARK; ROSEWOOD OIL

Derma E Acne Blemish Control Treatment Serum

Drug Facts

Active Ingredients

Salicylic Acid 1.9%

Purpose

Anti-Acne

Uses

- For the treatment of acne
- Helps keep skin clear of new acne, acne blemishes, acne pimples and blackheads

Warnings

For external use only

When using this product

- Skin irritation and dryness is more likely to occur if you use another topical acne medication at the same time. If irritation occurs, only use one topical acne medication at a time.
- Avoid contact with eyes. If contact occurs, flush thoroughly with water.

Keep out of reach of children.

If product is swallowed, get medical help or contact a Poison Control Center right away.

Directions

- SHAKE WELL
- Clean the skin thoroughly before applying this product
- Cover the entire affected area with a thin layer one to three times daily.
- Because excessive drying of the skin may occur, start with one application daily, then gradually increase to two or three times daily if needed or as directed by a doctor.
- If bothersome dryness or peeling occurs, reduce application to once a day or every other day.

Inactive ingredients

Purified Water, Glycerin, Hydroxypropyl Starch Phosphate (Sugar Starch), Salix Alba (Willow) Bark Extract, Epilobium Angustifolium (Canadian Willowherb) Extract, Aniba Rosodora (Rosewood) Wood Oil, Melaleuca Alternifolia (Tea Tree) Leaf Oil, Niacinamide (Vitamin B3), Organic Camellia Sinensis (Green Tea) Leaf Extract [Certified Organic Ingredients] , Aloe Barbadensis (Aloe Vera) Leaf Juice, Caffeine, Hamamelis Virginiana (Witch Hazel) Extract, Lavandula Angustifolia (Lavender) Oil, Carrageenan (Seaweed Derived), Citric Acid, Potassium Hydroxide, Polysorbate 20, Xanthan Gum, Potassium Sorbate, Phenoxyethanol, Ethylhexylglycerin.

Distributed by DERMA E®
Simi Valley, CA 93065, USA

PRINCIPAL DISPLAY PANEL - 60 mL Jar Box

ANTI-ACNE

100% VEGAN • SOY-FREE
ECO-ETHICAL
CRUELTY-FREE

DERMA • E

Acne Blemish
Control
Treatment
Serum

Active Salicylic Acid
Tea Tree Oil
Aloe Vera

reduces acne,
blackheads and breakouts

• DERMATOLOGIST •
RECOMMENDED

2 FL OZ / 60 mL